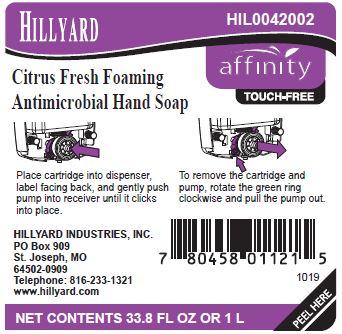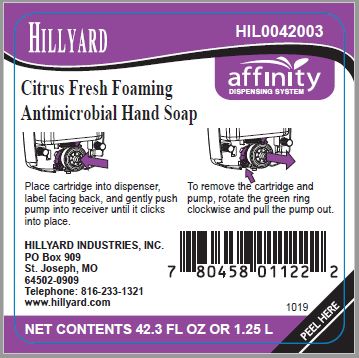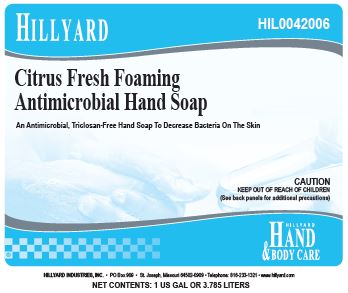 DRUG LABEL: Citrus Fresh Foaming Antimicrobial
NDC: 76402-420 | Form: LIQUID
Manufacturer: Hillyard GMP
Category: otc | Type: HUMAN OTC DRUG LABEL
Date: 20241231

ACTIVE INGREDIENTS: BENZALKONIUM CHLORIDE 0.13 g/100 mL
INACTIVE INGREDIENTS: WATER; COCAMIDOPROPYLAMINE OXIDE; GLYCERIN; PROPANEDIOL; BENZYL ALCOHOL; PHENOXYETHANOL; CETRIMONIUM CHLORIDE; LAURTRIMONIUM CHLORIDE; DIHYDROXYETHYL COCAMINE OXIDE; GLYCERETH-17 COCOATE; FD&C RED NO. 40; ALOE VERA LEAF; FD&C YELLOW NO. 6; CITRIC ACID MONOHYDRATE

Citrus Fresh Foaming Antimicrobial Hand Soap

Active Ingredients

Benzalkonium Chloride 0.13%

Purpose

Antimicrobial

Uses

- Helps reduce bacteria that potentially can cause disease
- Helps prevent cross-contamination by hand contact

Warnings

- For External Use Only
- Do not contaminate water, food or feed by storage and disposal.

Keep out of reach of children.

- In case of eye contact, flush with water for 15 minutes. If irritation persists, get medical attention. In case of accidental ingestion, seek medical attention or contact a poison control center immediately.

Directions

- Apply soap to palm of hand.
- Lather and scrub hands (including fingers, wrist, and cuticles) vigorously for 60 seconds.
- Rinse with water until all soap is removed from hands.
- Dry completely (incomplete drying may lead to chapped skin).
- Children under 6 years of age should be supervised when using this product.

Inactive Ingredients

Water, Cocamidopropylamine Oxide, Glycerin, Propanediol, Benzyl Alcohol, Phenoxyethanol, Fragrance, Cetrimonium Chloride, Laurtrimonium Chloride, Dihydroxyethyl Cocamine Oxide, Glycereth-17 Cocoate, Red 40, Aloe Barbadensis Leaf Juice, Yellow #6, Citric Acid.

Principal Display Panel – 1 Liter Label

Hillyard

Citrus Fresh Foaming Antimicrobial Hand Soap

HIL0042002

affinity
TOUCH-FREE

Place cartridge into dispenser, label facing back, and gently push pump into receiver until it clicks into place.

To remove the cartridge and pump, rotate the green ring clockwise and pull the pump out.

HILLYARD INDUSTRIES, INC.
PO Box 909
St. Joseph, MO
64502-0909
Telephone: 816-233-1321
www.hillyard.com

NET CONTENTS 33.8 FL OZ OR 1 L
PEEL HERE

Principal Display Panel – 1.25 Liter Label

Hillyard

Citrus Fresh Foaming Antimicrobial Hand Soap

HIL0042003

affinity
DISPENSING SYSTEM

Place cartridge into dispenser, label facing back, and gently push pump into receiver until it clicks into place.

To remove the cartridge and pump, rotate the green ring clockwise and pull the pump out.

HILLYARD INDUSTRIES, INC.
PO Box 909
St. Joseph, MO
64502-0909
Telephone: 816-233-1321
www.hillyard.com

NET CONTENTS 42.3 FL OZ OR 1.25 L
PEEL HERE

Principal Display Panel – 1 US Gallon Label

Hillyard

Citrus Fresh Foaming Antimicrobial Hand Soap
An Antimicrobial, Triclosan-Free Hand Soap To Decrease Bacteria On The Skin

HIL0042006

CAUTION
KEEP OUT OF REACH OF CHILDREN
(See back panels for additional precautions)

HILLYARD
Hand & BODY CARE

HILLYARD INDUSTRIES, INC. • PO Box 909 • St. Joseph, Missouri 64502-0909 • Telephone: 816-233-1321 • www.hillyard.com

NET CONTENTS: 1 US GAL OR 3.785 LITERS